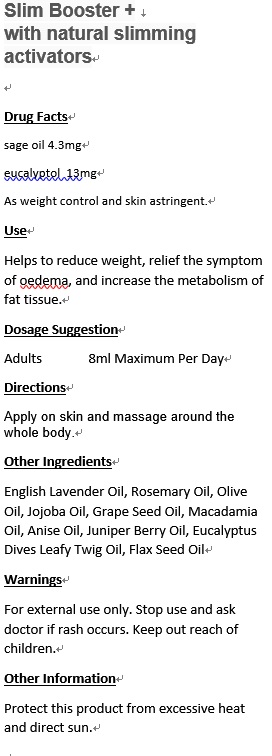 DRUG LABEL: Slim Booster
NDC: 70470-9013 | Form: OIL
Manufacturer: PHYTOPIA CO., LTD.
Category: otc | Type: HUMAN OTC DRUG LABEL
Date: 20160415

ACTIVE INGREDIENTS: SAGE OIL 4.3 mg/50 mL; EUCALYPTOL 13 mg/50 mL
INACTIVE INGREDIENTS: FLAX SEED 10.6 mg/50 mL; JUNIPER BERRY OIL 0.5 mL/50 mL; ANISE OIL 0.57 mL/50 mL; EUCALYPTUS DIVES LEAFY TWIG OIL 0.25 mL/50 mL; ENGLISH LAVENDER OIL 0.31 mL/50 mL; ROSEMARY OIL 0.31 mL/50 mL; OLIVE OIL 31.5 mL/50 mL; JOJOBA OIL 2.3 mL/50 mL; GRAPE SEED OIL 3.7 mL/50 mL; MACADAMIA OIL 10 mL/50 mL

Drug Facts

Sage oil 4.3mg

Eucalyptol 13mg

As weight control and skin astringent.

Use

Helps to reduce weight, relief the symptom of oedema, and increase the metabolism of fat tissue.

Dosage Suggestion

Adults 8ml Maximum Per Day

Directions

Apply on skin and massage around the whole body.

INACTIVE INGREDIENT

Other Ingredients

English Lavender Oil, Rosemary Oil, Olive Oil, Jojoba Oil, Grape Seed Oil, Macadamia Oil, Anise Oil, Juniper Berry Oil, Eucalyptus Dives Leafy Twig Oil, Flax Seed Oil

Warnings

For external use only. Stop use and ask doctor if rash occurs. Keep out reach of children.

Warnings

For external use only. Stop use and ask doctor if rash occurs. Keep out reach of children.

Other Information

Protect this product from excessive heat and direct sun.

PACKAGE LABEL

Slim Booster +
with natural slimming activators